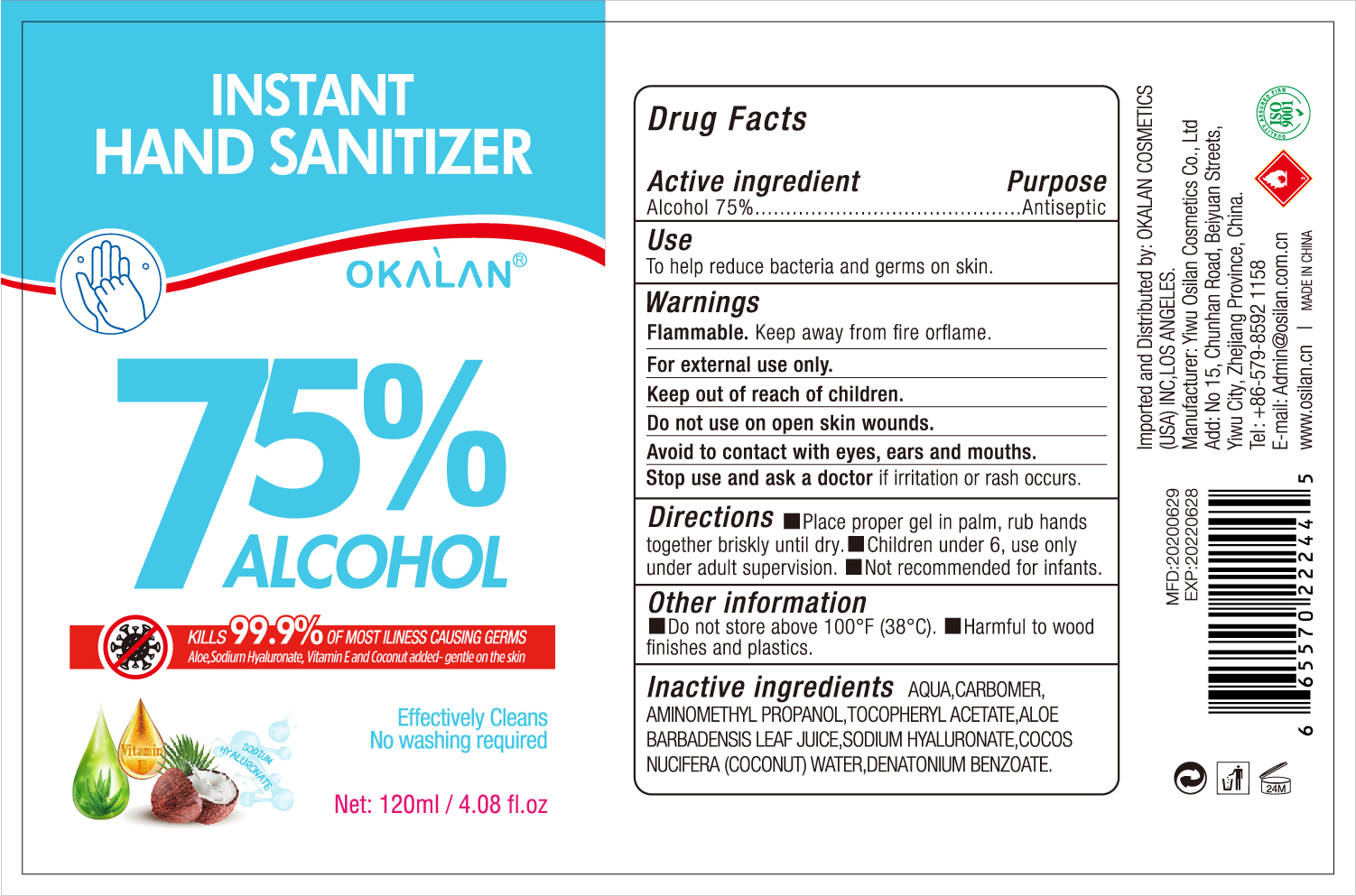 DRUG LABEL: INSTANT HAND SANITIZER
NDC: 78446-001 | Form: LIQUID
Manufacturer: YIWU OSILAN COSMETICS CO., LTD
Category: otc | Type: HUMAN OTC DRUG LABEL
Date: 20200525

ACTIVE INGREDIENTS: ALCOHOL 75 mL/100 mL
INACTIVE INGREDIENTS: COCONUT WATER 0.1 mL/100 mL; DENATONIUM BENZOATE 0.1 mL/100 mL; ALOE VERA LEAF 0.1 mL/100 mL; PEG-9 DIGLYCIDYL ETHER/SODIUM HYALURONATE CROSSPOLYMER 0.1 mL/100 mL; 5-NORBORNENE-2-METHYLOLACRYLATE 5 mL/100 mL; AMINOMETHYLPROPANOL 1 mL/100 mL; WATER; .ALPHA.-TOCOPHEROL ACETATE, DL- 0.1 mL/100 mL

INSTANT HAND SANITIZER

Active Ingredient

Alcohol 75% v/v.

Purpose

Purpose: Antiseptic

Use

To help reduce bacteria and germs on skin

Warnings

For external use only. Flammable. Keep away from heat or flame

Do not use on open skin wounds

WHEN USING

avoid to contact with eyes, ears and mouths

Stop use and ask a doctor if irritation or rash occurs.

Keep out of reach of children.

Directions

- Place proper gen in palm, rub hands together until dry.
- children under 6 , use only under adult supervision
- Not recommentde for infants

Other information

- do not store above 100℉(38℃) harmful to wood finishes and plastics

Inactive ingredients

AQUA，CARBOMER，AMINOMETHYL PROPANOL，TOCOPHERYL ACETATE，ALOE BARBADENSIS LEAF JUICE，SODIUM HYALURONATE，COCOS NUCIFERA (COCONUT) WATER，DENATONIUM BENZOATE